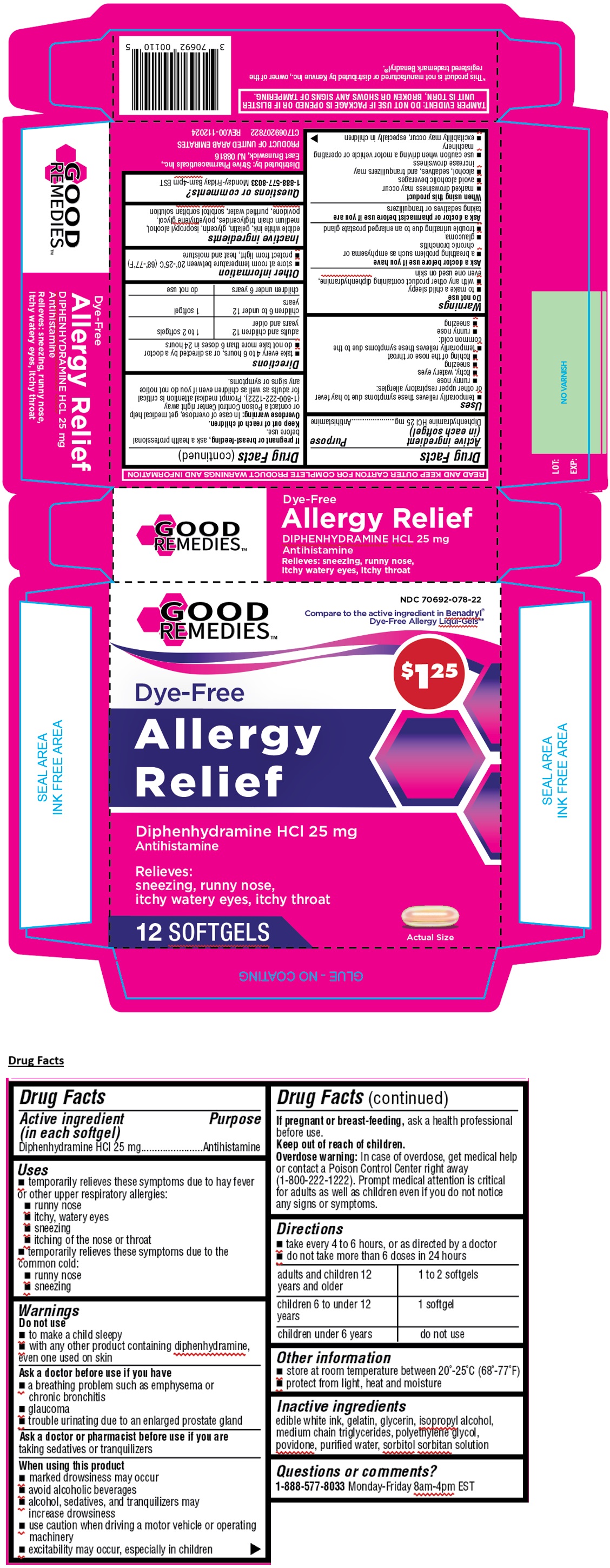 DRUG LABEL: GOOD REMEDIES Allergy Relief SOFTGEL
NDC: 70692-078 | Form: CAPSULE, LIQUID FILLED
Manufacturer: Strive Pharmaceuticals Inc.
Category: otc | Type: HUMAN OTC DRUG LABEL
Date: 20250122

ACTIVE INGREDIENTS: DIPHENHYDRAMINE HYDROCHLORIDE 25 mg/1 1
INACTIVE INGREDIENTS: GELATIN, UNSPECIFIED; GLYCERIN; ISOPROPYL ALCOHOL; MEDIUM-CHAIN TRIGLYCERIDES; POLYETHYLENE GLYCOL, UNSPECIFIED; POVIDONE, UNSPECIFIED; WATER; SORBITOL; SORBITAN

GOOD REMEDIESTM Allergy Relief SOFTGELS

Active ingredient (in each softgel)

Diphenhydramine HCl 25 mg

Purpose

Antihistamine

Uses

• temporarily relieves these symptoms due to hay fever or other upper respiratory allergies:
• runny nose
• itchy, watery eyes
• sneezing
• itching of the nose or throat
• temporarily relieves these symptoms due to the common cold:
• runny nose
• sneezing

Warnings

Do not use
• to make a child sleepy
• with any other product containing diphenhydramine, even one used on skin

Ask a doctor before use if you have
• a breathing problem such as emphysema or chronic bronchitis
• glaucoma
• trouble urinating due to an enlarged prostate gland

Ask a doctor or pharmacist before use if you are
taking sedatives or tranquilizers

When using this product
• marked drowsiness may occur
• avoid alcoholic beverages
• alcohol, sedatives, and tranquilizers may increase drowsiness
• use caution when driving a motor vehicle or operating machinery
• excitability may occur, especially in children

If pregnant or breast-feeding, ask a health professional before use.

Keep out of reach of children.

Overdose warning: In case of overdose, get medical help or contact a Poison Control Center right away (1-800-222-1222). Prompt medical attention is critical for adults as well as children even if you do not notice any signs or symptoms.

Directions

• take every 4 to 6 hours, or as directed by a doctor
• do not take more than 6 doses in 24 hours

adults and children 12 years and older | 1 to 2 softgels
children 6 to under 12 years | 1 softgel
children under 6 years | do not use

Other information

• store at room temperature between 20°-25°C (68°-77°F)
• protect from light, heat and moisture

Inactive ingredients

edible white ink, gelatin, glycerin, isopropyl alcohol, medium chain triglycerides, polyethylene glycol, povidone, purified water, sorbitol sorbitan solution

Questions or comments?

1-888-577-8033 Monday-Friday 8am-4pm EST

Compare to the active ingredient in Benadryl® Dye-Free Allergy Liqui-Gels®*

Dye-Free

Relieves:
sneezing, runny nose,
itchy watery eyes, itchy throat

READ AND KEEP OUTER CARTON FOR COMPLETE PRODUCT WARNINGS AND INFORMATION

Distributed by: Strive Pharmaceuticals Inc.,
East Brunswick, NJ 08816

PRODUCT OF UNITED ARAB EMIRATES

REV.00-112024

TAMPER EVIDENT: DO NOT USE IF PACKAGE IS OPENED OR IF BLISTER UNIT IS TORN, BROKEN OR SHOWS ANY SIGNS OF TAMPERING.

*This product is not manufactured or distributed by Kenvue Inc., owner of the registered trademark Benadryl®.